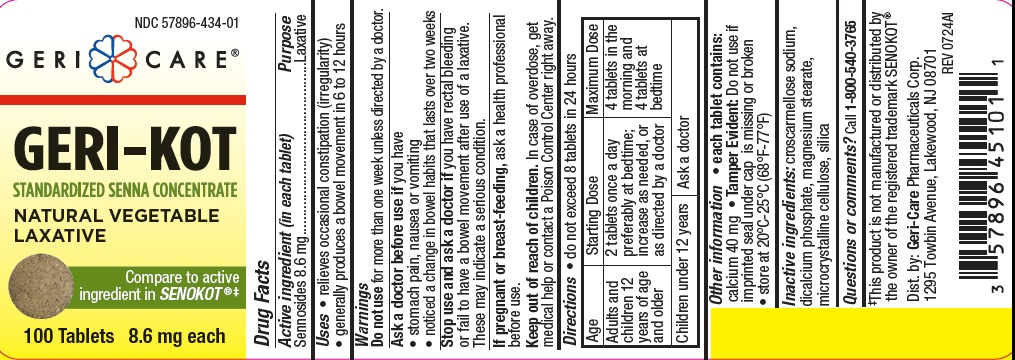 DRUG LABEL: Geri-kot
NDC: 57896-434 | Form: TABLET
Manufacturer: Geri-Care Pharmaceutical Corp
Category: otc | Type: HUMAN OTC DRUG LABEL
Date: 20241031

ACTIVE INGREDIENTS: SENNOSIDES 8.6 mg/1 1
INACTIVE INGREDIENTS: CELLULOSE, MICROCRYSTALLINE; CROSCARMELLOSE SODIUM; DIBASIC CALCIUM PHOSPHATE DIHYDRATE; MAGNESIUM STEARATE; SILICON DIOXIDE

GC 451AL 434

Active ingredient (in each tablet)

Sennosides 8.6 mg

Purpose

Laxative

Uses

- relieves occasional constipation (irregularity)

- generally produces bowel movement in 6 to 12 hours

Warnings

Do not use for more than one week unless directed by a doctor.

Ask a doctor before use if you have
• stomach pain, nausea or vomiting
• noticed a change in bowel habits that lasts over two weeks
Stop use and ask a doctor if you have rectal bleeding

or fail to have a bowel movement after use of a laxative.
These may indicate a serious condition.
If pregnant or breast-feeding, ask a health professional before use.

Keep out of reach of children. In case of overdose, get medical help or contact a Poison Control Center right away.

Directions

• do not exceed 8 tablets in 24 hours

Age | Starting Dose | Maximum Dose
adults and children 12 years of age and older | 2 tablets once a day preferably at bedtime; increase as needed, or as directed by a doctor | 4 tablets in the morning and 4 tablets at bedtime
children under 12 years | ask a doctor

Other information

- each tablet contains: calcium 40 mg
- Tamper Evident: Do not use if imprinted seal under cap is missing or broken
- store at 20°C-25°C (68°F-77°F)

Inactive ingredients

croscarmellose sodium, dicalcium phosphate, magnesium stearate, microcrystalline cellulose, silica